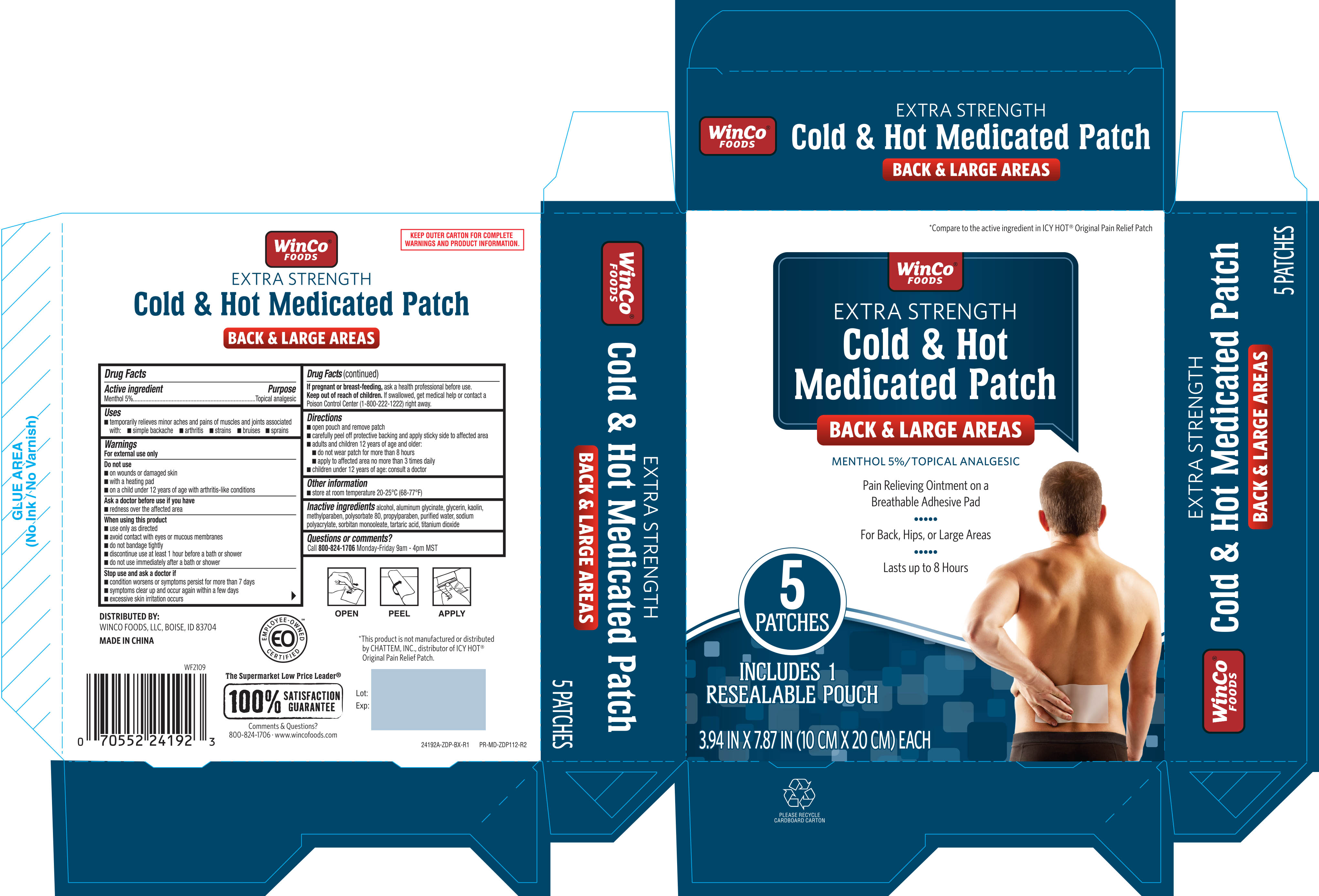 DRUG LABEL: Winco Cold and Hot Medicated Patch Large
NDC: 67091-914 | Form: PATCH
Manufacturer: WINCO FOODS, LLC
Category: otc | Type: HUMAN OTC DRUG LABEL
Date: 20251022

ACTIVE INGREDIENTS: MENTHOL 50 mg/1 1
INACTIVE INGREDIENTS: KAOLIN; METHYLPARABEN; POLYSORBATE 80; TITANIUM DIOXIDE; TARTARIC ACID; SORBITAN MONOOLEATE; WATER; GLYCERIN; ALCOHOL; SODIUM POLYACRYLATE (2500000 MW); PROPYLPARABEN; DIHYDROXYALUMINUM AMINOACETATE ANHYDROUS

Winco Cold & Hot Medicated Patch Large 5ct ZDP (24192A)

Active ingredient..................................Purpose

Methol 5%................................Topical Analgesic

Uses

temporarily relieves minor aches and pains of muscles and joints associated with:

- simple backache
- arthritis
- strains
- bruises
- sprains

Warnings

For external use only

DO NOT USE

- on wounds or damaged skin
- with a heating pad
- on a child under 12 years of age with arthritis-like conditions

Ask a doctor before use if you have

- redness over the affected area

When using this product

- use only as directed
- avoid contact with eyes or mucous membranes
- do not bandage tightly
- discontiue use at least 1 hour before a bath or shower
- do not use immedialtely after a bath or shower

Stop use and ask a doctor if

- condition worsens or symptoms persist for more than 7 days
- symptoms clear up and occur again within a few days
- excessive skin irritation occurs

PREGNANCY OR BREAST FEEDING

If pregnant or breast-feeding, ask a health professional before use.

Keep out of reach of children. If swallowed, get medical help or contact a Poison Control Center (1-800-222-1222) right away.

Directions

-open pouch and remove patch

-carefully peel off protective backing and apply sticky side to affected area

-adults and children 12 years of age and older:

- do not wear patch for more than 8 hours
- apply to affected area no more than 3 times daily

-children under 12 years of age: consult a doctor

Other Information

- store at room temperature 20-25ºC (68-77ºF)

INACTIVE INGREDIENT

Inactive ingredients alcohol, aluminum glycinate, glycerin, kaolin, methylparaben, polysorbate 80, propylparaben, purified water, sodium polyacrylate, sorbitan monooleate, tartaric acid, titanium dioxide

DOSAGE AND ADMINISTRATION

Distributed By:

WINCO FOODS, LLC,

BOISE, ID 83704

MADE IN CHINA